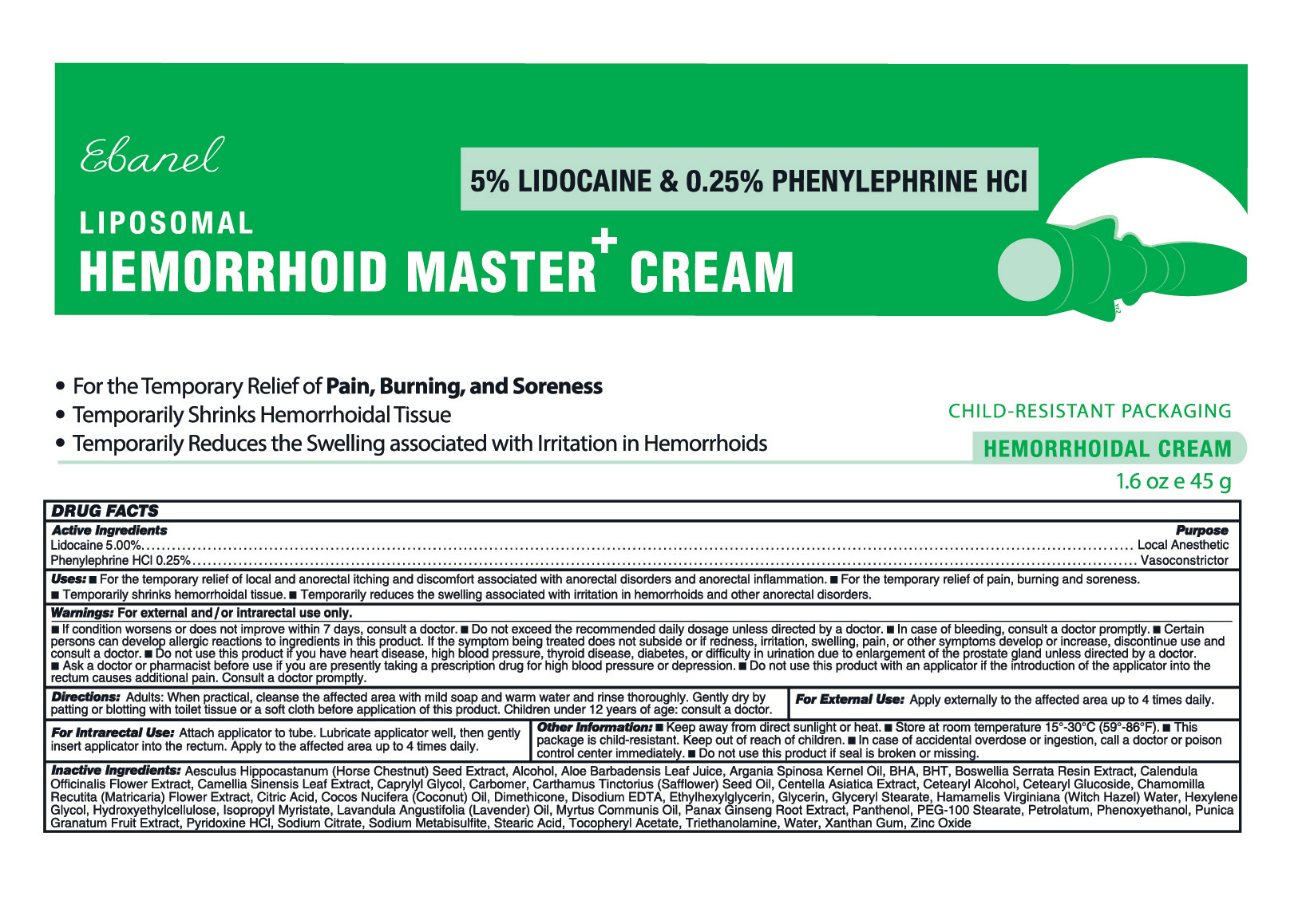 DRUG LABEL: Hemorrohoid Master Cream
NDC: 72654-038 | Form: CREAM
Manufacturer: Ebanel Laboratories, Inc.
Category: otc | Type: HUMAN OTC DRUG LABEL
Date: 20250606

ACTIVE INGREDIENTS: LIDOCAINE 50 mg/1 g; PHENYLEPHRINE HYDROCHLORIDE 2.5 mg/1 g
INACTIVE INGREDIENTS: DISODIUM EDTA-COPPER; ALCOHOL; CARBOMER; XANTHAN GUM; CHAMOMILE; WITCH HAZEL; SODIUM CITRATE; STEARIC ACID; TRIETHANOLAMINE; .ALPHA.-TOCOPHEROL ACETATE, D-; INDIAN FRANKINCENSE; HEXYLENE GLYCOL; PEG-100 STEARATE; LAVANDULA ANGUSTIFOLIA (LAVENDER) OIL; CITRIC ACID; POMEGRANATE; CAPRYLYL GLYCOL; BHT; CENTELLA ASIATICA LEAF; DIMETHICONE; ARGANIA SPINOSA KERNEL OIL; CETEARYL ALCOHOL; ALOE BARBADENSIS LEAF JUICE; CETEARYL GLUCOSIDE; SODIUM METABISULFITE; BHA; ETHYLHEXYLGLYCERIN; PANAX GINSENG ROOT; PYRIDOXINE HCL; HORSE CHESTNUT; ZINC OXIDE; GLYCERYL STEARATE SE; PANTHENOL; WATER; ISOPROPYL MYRISTATE; CARTHAMUS TINCTORIUS (SAFFLOWER) SEED OIL; CALENDULA OFFICINALIS FLOWER; CAMELLIA SINENSIS VAR. ASSAMICA WHOLE; COCOS NUCIFERA (COCONUT) OIL; HYDROXYETHYLCELLULOSE; PETROLATUM; PHENOXYETHANOL; GLYCERIN; MYRTUS COMMUNIS OIL

Active Ingredients

Lidocaine 5.00%

Phenylephrine HCl 0.25%

Directions

■ Adults: When practical, cleanse the affected area with mild soap and warm water and rinse thoroughly. Gently dry by patting or blotting with toilet tissue or a soft cloth before application of this product. Children under 12 years of age: consult a doctor.

■ For External Use: Apply externally to the affected area up to 4 times daily.

■ For Intrarectal use: Attach applicator to tube. Lubricate applicator well, then gently insert applicator into the rectum. Apply to the affected area up to 4 times daily.

Warnings: For external and / or intrarectal use only.

■ If condition worsens or does not improve within 7 days, consult a doctor.

■ Do not exceed the recommended daily dosage unless directed by a doctor.

■ In case of bleeding, consult a doctor promptly.

■ Certain persons can develop allergic reactions to ingredients in this product. If the symptom being treated does not subside or if redness, irritation, swelling, pain, or other symptoms develop or increase, discontinue use and consult a doctor.

■ Do not use this product if you have heart disease, high blood pressure, thyroid disease, diabetes, or difficulty in urination due to enlargement of the prostate gland unless directed by a doctor.

■ Ask a doctor or pharmacist before use if you are presently taking a prescription drug for high blood pressure or depression.

■ Do not use this product with an applicator if the introduction of the applicator into the rectum causes additional pain. Consult a doctor promptly.

Uses

■ For the temporary relief of local and anorectal itching and discomfort associated with anorectal disorders and anorectal inflammation.

■ For the temporary relief of pain, burning and soreness.

■ Temporarily shrinks hemorrhoidal tissue.

■ Temporarily reduces the swelling associated with irritation in hemorrhoids and other anorectal disorders.

Other Information

■ Keep away from direct sunlight or heat.

■ Store at room temperature 15°-30°C (59°-86°F).

■ This package is child-resistant. Keep out of reach of children.

■ In case of accidental overdose or ingestion, call a doctor or poison control center immediately.

■ Do not use this product if seal is broken or missing.

Inactive Ingredients

Aesculus Hippocastanum (Horse Chestnut) Seed Extract, Alcohol, Aloe Barbadensis Leaf Juice, Argania Spinosa Kernel Oil, BHA, BHT, Boswellia Serrata Resin Extract, Calendula Officinalis Flower Extract, Camellia Sinensis Leaf Extract, Caprylyl Glycol, Carbomer, Carthamus Tinctorius (Safflower) Seed Oil, Centella Asiatica Extract, Cetearyl Alcohol, Cetearyl Glucoside, Chamomilla Recutita (Matricaria) Flower Extract, Citric Acid, Cocos Nucifera (Coconut) Oil, Dimethicone, Disodium EDTA, Ethylhexylglycerin, Glycerin, Glyceryl Stearate, Hamamelis Virginiana (Witch Hazel) Water, Hexylene Glycol, Hydroxyethylcellulose, Isopropyl Myristate, Lavandula Angustifolia (Lavender) Oil, Myrtus Communis Oil, Panax Ginseng Root Extract, Panthenol, PEG-100 Stearate, Petrolatum, Phenoxyethanol, Punica Granatum Fruit Extract, Pyridoxine HCl, Sodium Citrate, Sodium Metabisulfite, Stearic Acid, Tocopheryl Acetate, Triethanolamine, Water, Xanthan Gum, Zinc Oxide

Purpose

Local Anesthetic

Vasoconstrictor